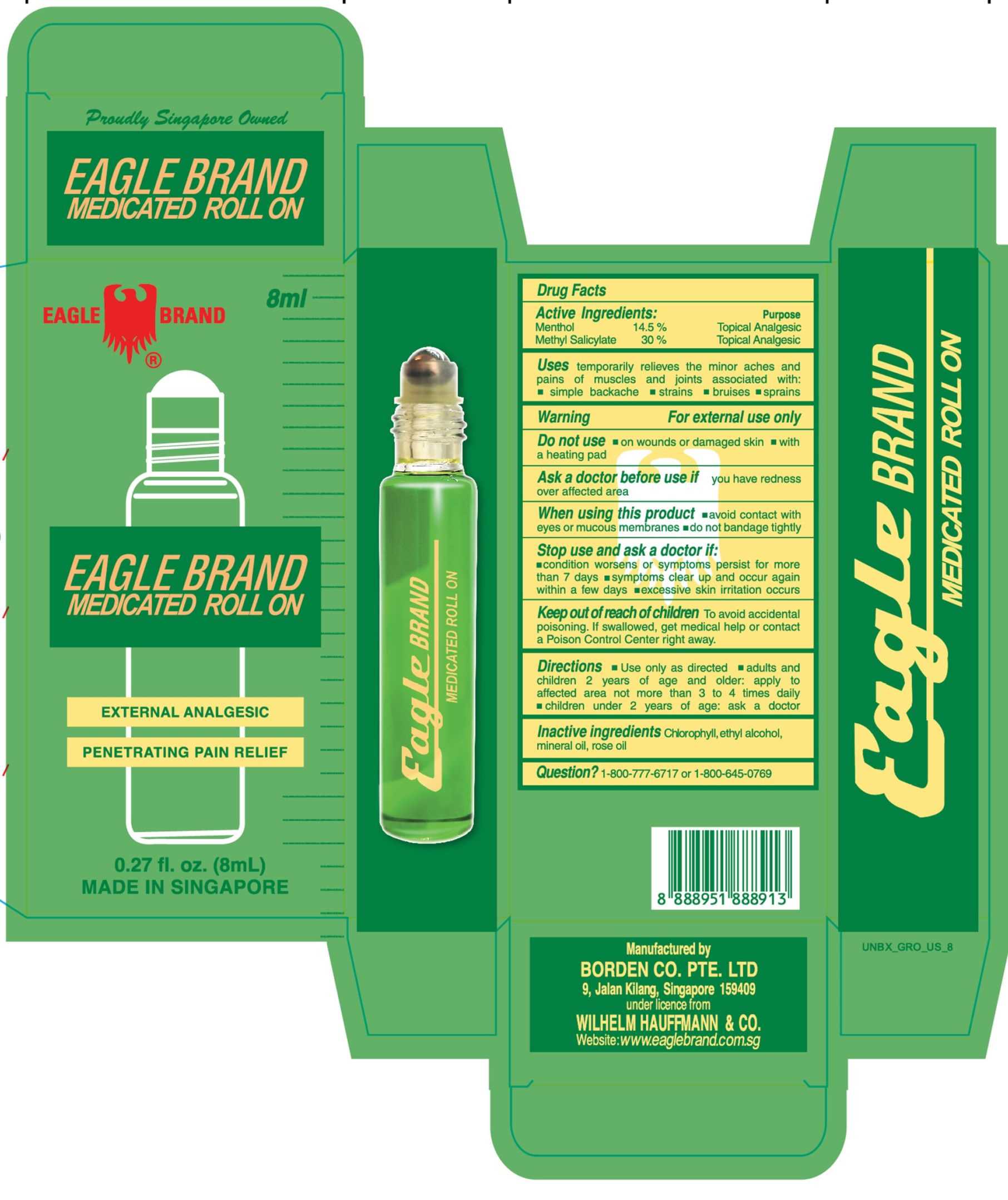 DRUG LABEL: Eagle
NDC: 43405-005 | Form: OIL
Manufacturer: Borden Company (Private) Limited
Category: otc | Type: HUMAN OTC DRUG LABEL
Date: 20250410

ACTIVE INGREDIENTS: MENTHOL 14.5 g/100 mL; METHYL SALICYLATE 30 g/100 mL
INACTIVE INGREDIENTS: ALCOHOL; MINERAL OIL; ROSE OIL; CHLOROPHYLL

Eagle Brand Medicated Oil Rollon

Active Ingredients

Menthol 14.5%
Methyl Salicylate 30%

Purpose

Topical Analgesic

Topical Analgesic

Uses

temporarily relieves the minor aches and pains of muscle and joint associated with : ■simple backache ■ strains ■ bruises ■ sprains

Warning

For external use only

Do not use

■ on woulds or damaged skin ■ with a heating pad

When using this product

■ avoid contact with eyes or mucous membranes

■ do not bandage tightly

Stop use and ask a doctor if

■ condition worsens or symptoms persist for more than 7 days ■ symptoms clear up and occur again within a few days ■ excessive skin irritation occurs

Keep this drug out of reach of children

To avoid accidental poisoning, if swallowed, get medical help or contact a Poison Control Center right away.

Directions

■ Use only as directed ■ adults and children 2 years and older: apply to affected area not more than 3 to 4 time daily. ■ children under 2 years of age: ask a doctor

Inactive ingredients

Chlorophyll, ethyl alcohol, mineral oil, rose oil

Question?

1-800-777-6717 or 1-800-645-0789

Package Label

8ml NDC: 43405-005-08